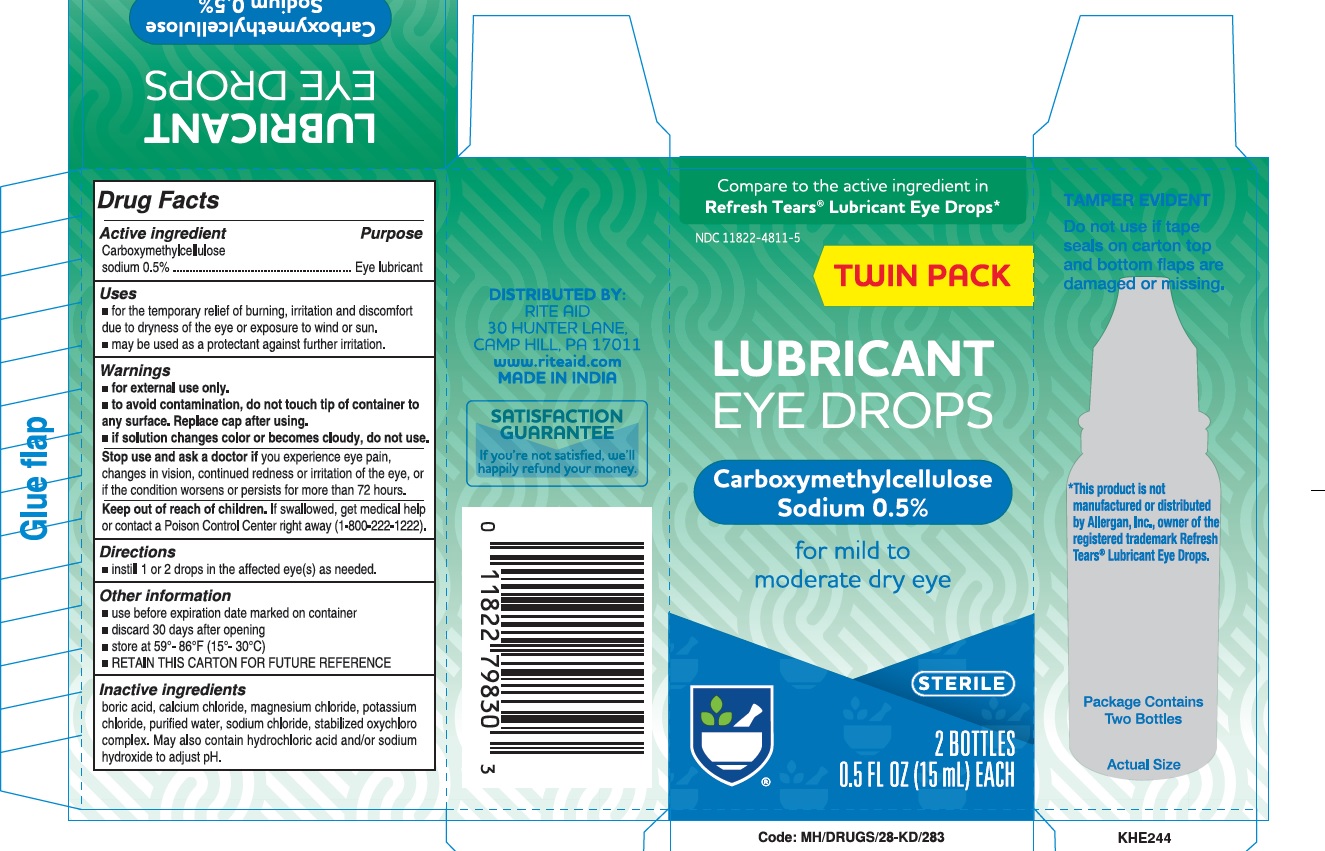 DRUG LABEL: Lubricant Drops
NDC: 11822-9707 | Form: SOLUTION/ DROPS
Manufacturer: RITE AID
Category: otc | Type: HUMAN OTC DRUG LABEL
Date: 20220608

ACTIVE INGREDIENTS: CARBOXYMETHYLCELLULOSE SODIUM 5 mg/1 mL
INACTIVE INGREDIENTS: BORIC ACID; CALCIUM CHLORIDE; MAGNESIUM CHLORIDE; POTASSIUM CHLORIDE; WATER; SODIUM CHLORITE; SODIUM CHLORIDE; HYDROCHLORIC ACID; SODIUM HYDROXIDE

Rite Aid
Lubricant Eye Drops

Active ingredient

Carboxymethylcellulose sodium 0.5%

Purpose

Eye lubricant

Uses

- For the temporary relief of burning, irritation, and discomfort due to dryness of the eye or exposure to wind or sun.
- May be used as a protectant against further irritation.

Warnings

- For external use only.
- To avoid contamination, do not touch tip of container to any surface. Replace cap after using.
- If solution changes color or becomes cloudy, do not use.

Stop use and ask a doctor if

you experience eye pain, changes in vision, continued redness or irritation of the eye, or if the condition worsens or persists for more than 72 hours.

Keep out of reach of children.

If swallowed, get medical help or contact a Poison Control Center right away.

Directions

Instill 1 or 2 drops in the affected eye(s) as needed.

Other information

- Use before expiration date marked on the container.
- Discard 30 days after opening
- Store at 59°-86°F (15°-30°C).
- RETAIN THIS CARTON FOR FUTURE REFERENCE.

Inactive ingredients

Boric acid; calcium chloride; magnesium chloride; potassium chloride; purified water; stabilized oxychloro complex; and sodium chloride. May also contain hydrochloric acid and/or sodium hydroxide to adjust pH.